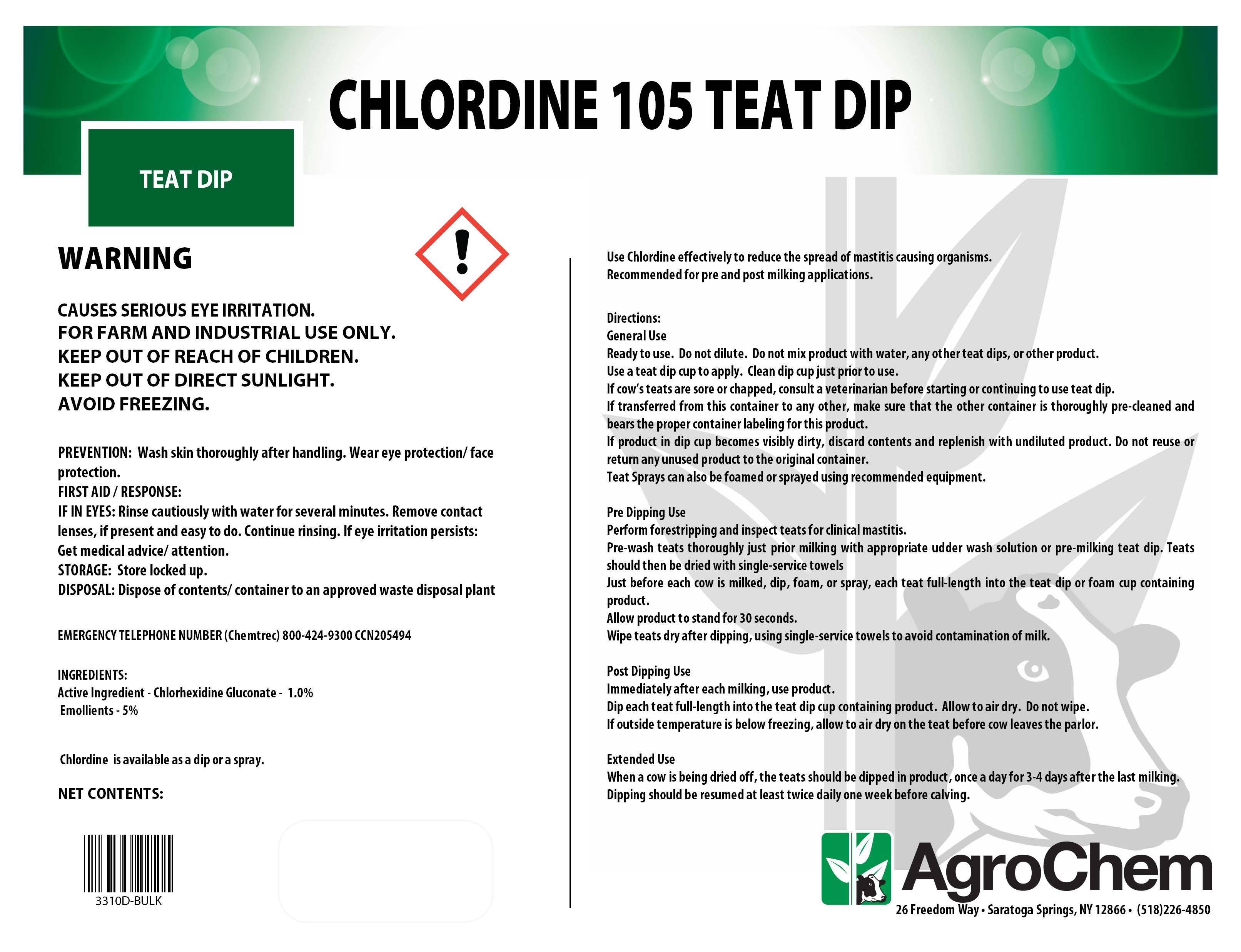 DRUG LABEL: Chlordine 105 Teat Dip
NDC: 17307-3334 | Form: SOLUTION
Manufacturer: AgroChem USA, LLC
Category: animal | Type: OTC ANIMAL DRUG LABEL
Date: 20241213

ACTIVE INGREDIENTS: CHLORHEXIDINE GLUCONATE 0.01 kg/1 kg
INACTIVE INGREDIENTS: NONOXYNOL-12 0.01 kg/1 kg; GLYCERIN 0.05 kg/1 kg

Chlordine 105 Teat Dip

DESCRIPTION

CHLORDINE 105 TEAT DIP

WARNING

CAUSES SERIOUS EYE IRRITATION.

FOR FARM AND INDUSTRIAL USE ONLY.

KEEP OUT OF REACH OF CHILDREN.

KEEP OUT OF DIRECT SUNLIGHT.

AVOID FREEZING.

PREVENTION: Wash skin thoroughly after handling. Wear eye protection/ face protection.

FIRST AID / RESPONSE:

IF IN EYES: Rinse cautiously with water for several minutes. Remove contact lenses, if present and easy to do. Continue rinsing. If eye irritation persists: Get medical advice/ attention.

STORAGE: Store locked up.

DISPOSAL: Dispose of contents/ container to an approved waste disposal plant

EMERGENCY TELEPHONE NUMBER (Chemtrec) 800-424-9300 CCN205494

ACTIVE INGREDIENT

INGREDIENTS:

Active Ingredient - Chlorhexidine Gluconate - 1.0%

Emollients - 5%

INSTRUCTIONS FOR USE

Use Chlordine effectively to reduce the spread of mastitis causing organisms.

Recommended for pre and post milking applications.

Directions:

General Use

Ready to use. Do not dilute. Do not mix product with water, any other teat dips, or other product.

Use a teat dip cup to apply. Clean dip cup just prior to use.

If cow’s teats are sore or chapped, consult a veterinarian before starting or continuing to use teat dip.

If transferred from this container to any other, make sure that the other container is thoroughly pre-cleaned and bears the proper container labeling for this product.

If product in dip cup becomes visibly dirty, discard contents and replenish with undiluted product. Do not reuse or return any unused product to the original container.

Teat Sprays can also be foamed or sprayed using recommended equipment.

Pre Dipping Use

Perform forestripping and inspect teats for clinical mastitis.

Pre-wash teats thoroughly just prior milking with appropriate udder wash solution or pre-milking teat dip. Teats should then be dried with single-service towels

Just before each cow is milked, dip, foam, or spray, each teat full-length into the teat dip or foam cup containing product.

Allow product to stand for 30 seconds.

Wipe teats dry after dipping, using single-service towels to avoid contamination of milk.

Post Dipping Use

Immediately after each milking, use product.

Dip each teat full-length into the teat dip cup containing product. Allow to air dry. Do not wipe.

If outside temperature is below freezing, allow to air dry on the teat before cow leaves the parlor.

Extended Use

When a cow is being dried off, the teats should be dipped in product, once a day for 3-4 days after the last milking.

Dipping should be resumed at least twice daily one week before calving.